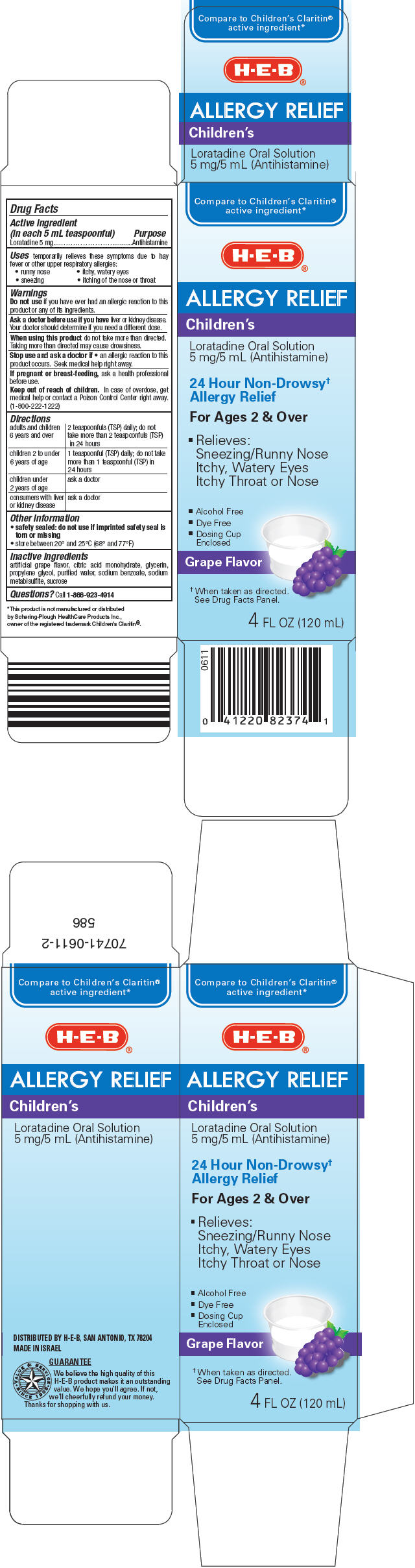 DRUG LABEL: Allergy Relief 
NDC: 37808-085 | Form: SOLUTION
Manufacturer: H E B
Category: otc | Type: HUMAN OTC DRUG LABEL
Date: 20121108

ACTIVE INGREDIENTS: Loratadine 5 mg/5 mL
INACTIVE INGREDIENTS: citric acid monohydrate; glycerin; propylene glycol; water; sodium benzoate; sodium metabisulfite; sucrose

Allergy Relief
Children's

Drug Facts

Active ingredient (in each 5 mL teaspoonful)

Loratadine 5 mg

Purpose

Antihistamine

Uses

temporarily relieves these symptoms due to hay fever or other upper respiratory allergies:

- runny nose
- sneezing
- itchy, watery eyes
- itching of the nose or throat

Warnings

Do not use if you have ever had an allergic reaction to this product or any of its ingredients.

Ask a doctor before use if you have liver or kidney disease. Your doctor should determine if you need a different dose.

When using this product do not take more than directed. Taking more than directed may cause drowsiness.

Stop use and ask a doctor if

- an allergic reaction to this product occurs. Seek medical help right away.

PREGNANCY OR BREAST FEEDING

If pregnant or breast-feeding, ask a health professional before use.

Keep out of reach of children. In case of overdose, get medical help or contact a Poison Control Center right away. (1-800-222-1222)

Directions

adults and children 6 years and over | 2 teaspoonfuls (TSP) daily; do not take more than 2 teaspoonfuls (TSP) in 24 hours
children 2 to under 6 years of age | 1 teaspoonful (TSP) daily; do not take more than 1 teaspoonful (TSP) in 24 hours
children under 2 years of age | ask a doctor
consumers with liver or kidney disease | ask a doctor

Other information

- safety sealed: do not use if imprinted safety seal is torn or missing
- store between 20° and 25°C (68° and 77°F)

Inactive ingredients

artificial grape flavor, citric acid monohydrate, glycerin, propylene glycol, purified water, sodium benzoate, sodium metabisulfite, sucrose

Questions?

Call 1-866-923-4914

DISTRIBUTED BY H-E-B, SAN ANTONIO, TX 78204

PRINCIPAL DISPLAY PANEL - 120 mL Bottle Carton

Compare to Children's Claritin®
active ingredient*

H-E-B®

ALLERGY RELIEF

Children's

Loratadine Oral Solution
5 mg/5 mL (Antihistamine)

24 Hour Non-Drowsy†
Allergy Relief

For Ages 2 & Over

- Relieves:
  Sneezing/Runny Nose
  Itchy, Watery Eyes
  Itchy Throat or Nose

- Alcohol Free
- Dye Free
- Dosing Cup
  Enclosed

Grape Flavor

† When taken as directed.
See Drug Facts Panel.

4 FL OZ (120 mL)